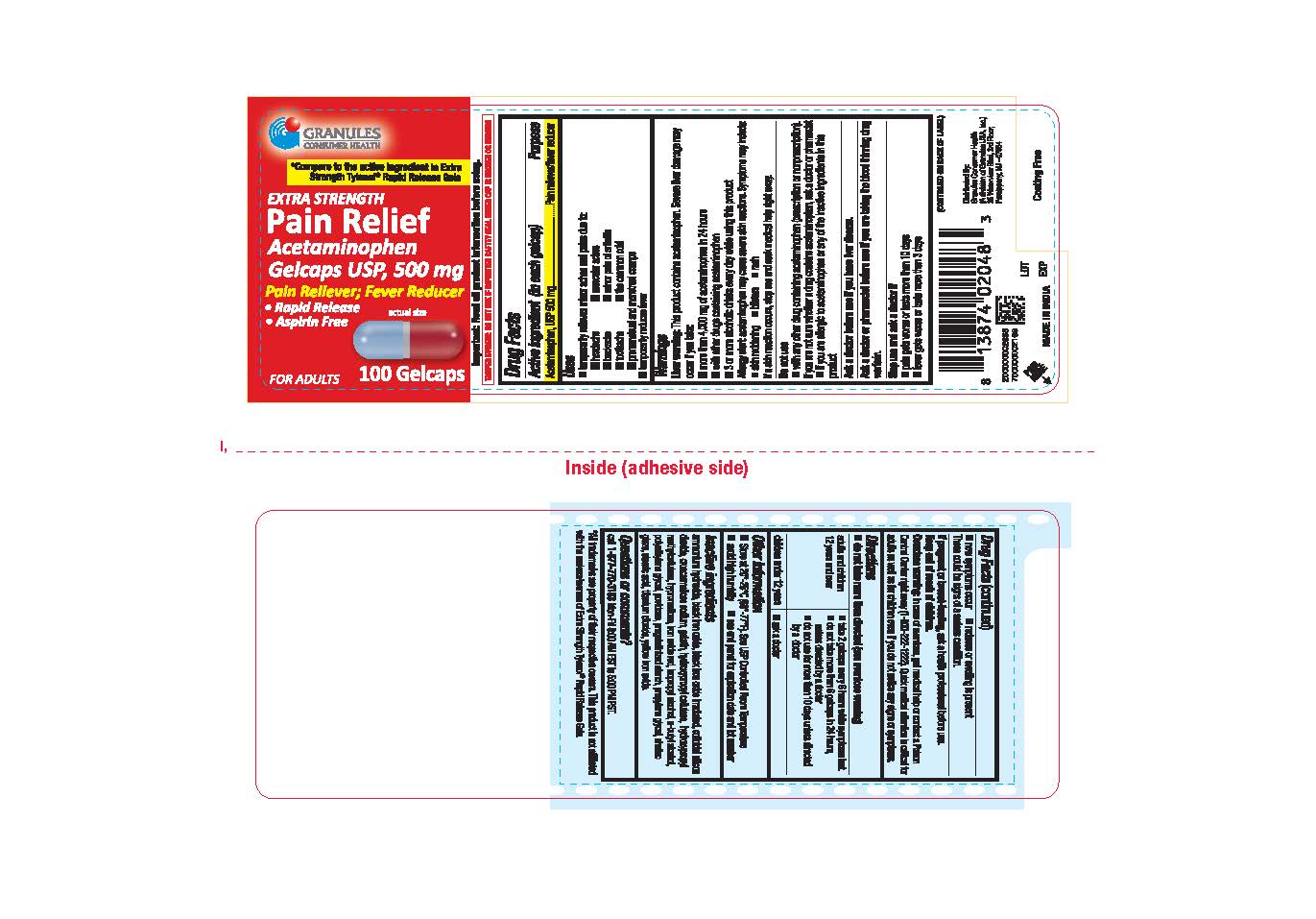 DRUG LABEL: Acetaminophen
NDC: 69848-008 | Form: TABLET
Manufacturer: Granules USA, Inc
Category: otc | Type: HUMAN OTC DRUG LABEL
Date: 20251222

ACTIVE INGREDIENTS: ACETAMINOPHEN 500 mg/1 1
INACTIVE INGREDIENTS: FD&C RED NO. 40; FD&C BLUE NO. 1; HYDROXYPROPYL CELLULOSE (1600000 WAMW); D&C RED NO. 33; AMMONIA; GELATIN; FERRIC OXIDE RED; POLYETHYLENE GLYCOL 400; ISOPROPYL ALCOHOL; PROPYLENE GLYCOL; SHELLAC; CROSCARMELLOSE SODIUM; FERROSOFERRIC OXIDE; SILICON DIOXIDE; HYPROMELLOSE 2910 (3 MPA.S); BUTYL ALCOHOL; POVIDONE K30; STARCH, CORN; STEARIC ACID; TITANIUM DIOXIDE; FERRIC OXIDE YELLOW; FD&C YELLOW NO. 6

EXTRA STRENGTH
Pain Relief
Acetaminophen Gelcaps USP, 500 mg
Pain reliever; Fever reducer
Rapid Release
Aspirin free

Active ingredient

(in each Gelcap)

Acetaminophen, USP 500 mg

Purpose

Pain reliever/fever reducer

Uses

■ temporarily relieves minor aches and pains due to:

■ headache

■ muscular aches

■ backache

■ minor pain of arthritis

■ toothache

■ he common cold

■ premenstrual and menstrual cramps

■ temporarily reduces fever

Liver warning

This product contains acetaminophen. Severe liver damage may occur if you take:

■ more than 4,000 mg of acetaminophen in 24 hours

■ with other drugs containing acetaminophen

■ 3 or more alcoholic drinks every day while using this product

Allergy alert

acetaminophen may cause severe skin reactions. Symptoms may include:

■ skin reddening

■ blisters

■ rash

If a skin reaction occurs, stop use and seek medical help right away.

Do not use

■ with any other drug containing acetaminophen (prescription or nonprescription). If you are not sure whether a drug contains acetaminophen, ask a doctor or pharmacist

■ if you have ever had an allergic reaction to this product or any of its ingredients

Ask a doctor before use if you have

liver disease.

Ask a doctor or pharmacist before use if you are

taking the blood thinning drug warfarin.

Stop use and ask a doctor if

■ pain gets worse or lasts more than 10 days

■ fever gets worse or lasts more than 3 days

■ new symptoms occur

■ redness or swelling is present

These could be signs of a serious condition.

If pregnant or breast-feeding,

ask a health professional before use.

Keep out of the reach of children.

In case of accidental overdose, get medical help or contact a Poison Control Center (1-800-222-1222) right away. Prompt medical attention is critical for adults as well as for children even if you do not notice any signs or symptoms.

overdose warning

In case of accidental overdose, get medical help or contact a Poison Control Centerright away (1-800-222-1222). Quick medical attention is critical for adults as well as for children even if you do not notice any signs or symptoms.

Directions

■ do not take more than directed (see overdose warning)

adults and children 12 years and over

■ take 2 gelcaps every 6 hours while symptoms last

■ do not take more than 6 gelcaps in 24 hours, unless directed by a doctor

■ do not take more than 10 days unless directed by a doctor

children under 12 years

■ ask a doctor

Other information

■ store at 20°-25°C (68°-77°F). See USP Controlled Room Temperature

■ avoid high humidity

■ see end panel for lot number and expiration date

Inactive ingredients

ammonium hydroxide, black iron oxide, black iron oxide irradiated, colloidal silicon dioxide, croscarmellose sodium, gelatin, hydroxypropyl cellulose, hydroxypropyl methyl cellulose, hypromellose, iron oxide red, isopropyl alcohol, n-butyl alcohol, polyethylene glycol, povidone, pregelatinized starch, propylene glycol, shellac glaze, stearic acid, titanium dioxide, yellow iron oxide.

Questions or comments?

call 1-877-770-3183 Mon-Fri 8:00 AM EST to 5:00 PM PST.